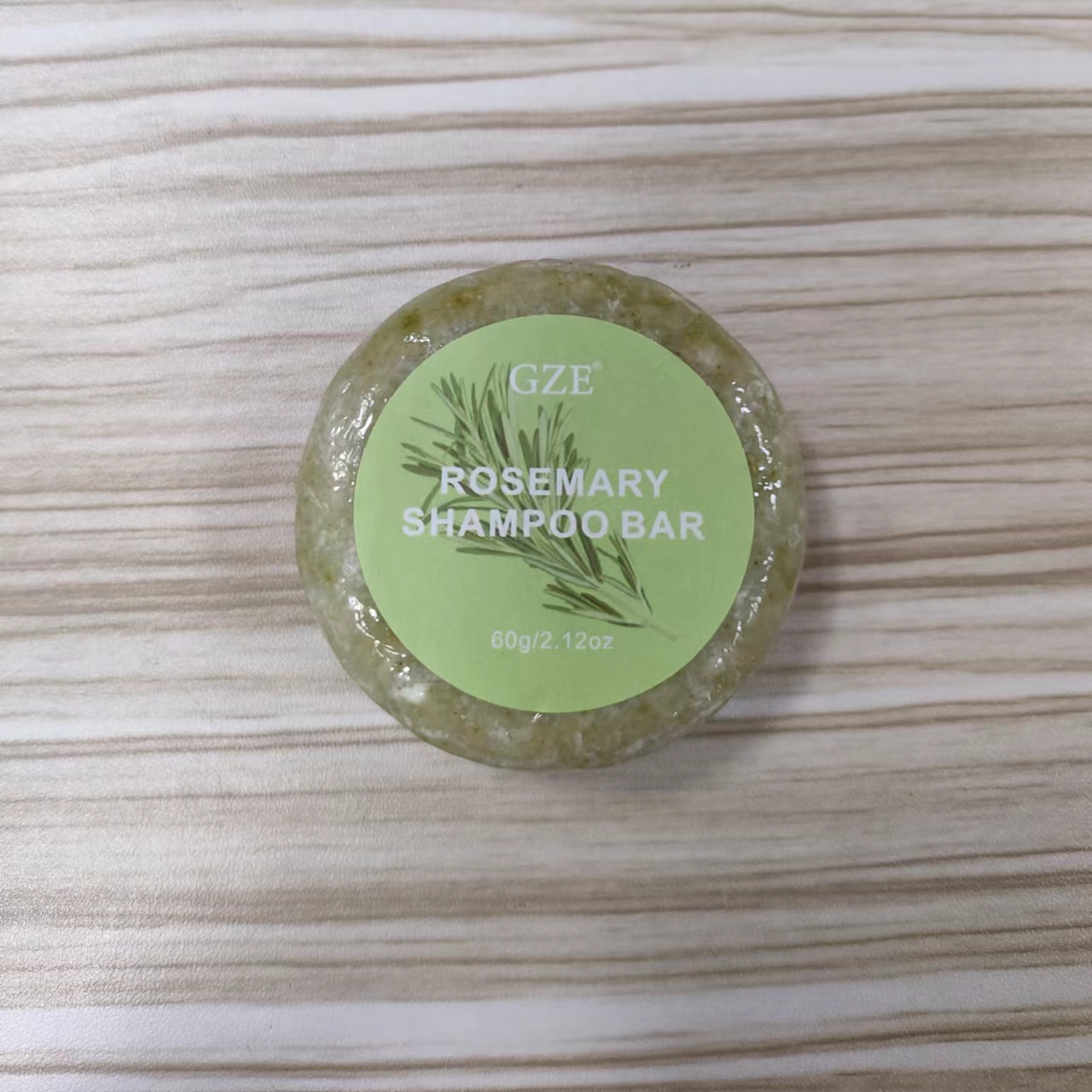 DRUG LABEL: GZE Rosemary ShampooBar
NDC: 74458-125 | Form: SOAP
Manufacturer: Guangzhou Yilong Cosmetics Co., Ltd
Category: otc | Type: HUMAN OTC DRUG LABEL
Date: 20241009

ACTIVE INGREDIENTS: ROSEMARY OIL 5 g/100 g
INACTIVE INGREDIENTS: COCAMIDOPROPYL BETAINE; RICE BRAN OIL; CITRIC ACID MONOHYDRATE; CYMBOPOGON SCHOENANTHUS OIL; LIME OIL, COLD PRESSED; EUCALYPTUS OIL; POTASSIUM SORBATE; WATER; BITTER ORANGE OIL; SODIUM BENZOATE

ACTIVE INGREDIENT

rosemary oil 5%

INACTIVE INGREDIENT

Water

Citric Acid

Oryza Sativa (Rice) Bran Oil

Cocamidopropyl Betaine

Cymbopogon Schoenanthus Oil

Citrus Aurantifolia (Lime) Oil

Citrus Aurantium Amara (Bitter Orange) Peel Oil

Eucalyptus Globulus Leaf Oil

Sodium Benzoate

Potassium Sorbate

PURPOSE

Dandruff.

INDICATIONS AND USAGE

Wet your hair and the bar, slide the bar down your hair from roots to tips 4 - 5 times. Massaae into your hair and feel the foamy goodness! Then rinse thoroughly with water.

WARNINGS

For external use only.

Stop use and ask a doctor if rash occurs.

Do not use on damaged or broken skin.

When using this product keep out of eyes. Rinse with water to remove.

Keep out of reach of children. If swallowed, get medical help or contact a Poison Control Center right away.

DOSAGE AND ADMINISTRATION

Wet your hair and the bar, slide the bar down your hair from roots to tips 4 - 5 times. Massaae into your hair and feel the foamy goodness! Then rinse thoroughly with water